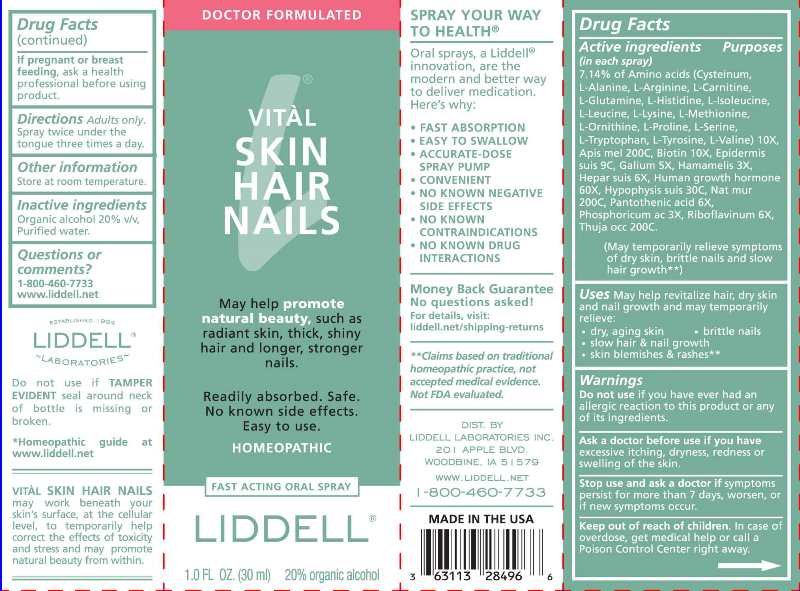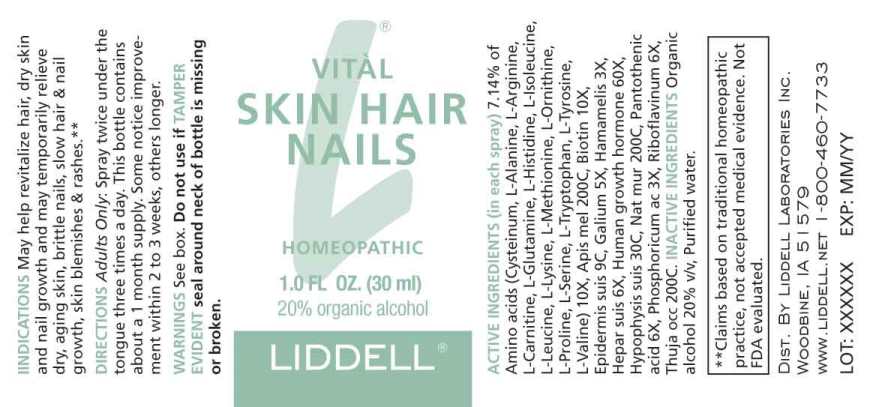 DRUG LABEL: Vital Skin Hair Nails
NDC: 50845-0278 | Form: SPRAY
Manufacturer: Liddell Laboratories, Inc.
Category: homeopathic | Type: HUMAN OTC DRUG LABEL
Date: 20230615

ACTIVE INGREDIENTS: ALANINE 10 [hp_X]/1 mL; ARGININE 10 [hp_X]/1 mL; LEVOCARNITINE 10 [hp_X]/1 mL; CYSTEINE 10 [hp_X]/1 mL; GLUTAMINE 10 [hp_X]/1 mL; HISTIDINE 10 [hp_X]/1 mL; ISOLEUCINE 10 [hp_X]/1 mL; LEUCINE 10 [hp_X]/1 mL; LYSINE 10 [hp_X]/1 mL; METHIONINE 10 [hp_X]/1 mL; ORNITHINE 10 [hp_X]/1 mL; PROLINE 10 [hp_X]/1 mL; SERINE 10 [hp_X]/1 mL; TRYPTOPHAN 10 [hp_X]/1 mL; TYROSINE 10 [hp_X]/1 mL; VALINE 10 [hp_X]/1 mL; APIS MELLIFERA 200 [hp_C]/1 mL; BIOTIN 10 [hp_X]/1 mL; SUS SCROFA SKIN 9 [hp_C]/1 mL; GALIUM APARINE WHOLE 5 [hp_X]/1 mL; HAMAMELIS VIRGINIANA ROOT BARK/STEM BARK 3 [hp_X]/1 mL; PORK LIVER 6 [hp_X]/1 mL; SOMATROPIN 60 [hp_X]/1 mL; SUS SCROFA PITUITARY GLAND 30 [hp_C]/1 mL; SODIUM CHLORIDE 200 [hp_C]/1 mL; PANTOTHENIC ACID 6 [hp_X]/1 mL; PHOSPHORIC ACID 3 [hp_X]/1 mL; RIBOFLAVIN 6 [hp_X]/1 mL; THUJA OCCIDENTALIS LEAFY TWIG 200 [hp_C]/1 mL
INACTIVE INGREDIENTS: WATER; ALCOHOL

DRUG FACTS:

ACTIVE INGREDIENTS:

(in each spray) 7.14% of Cysteinum 10X, L-Alanine 10X, L-Arginine 10X, L-Carnitine 10X, L-Glutamine 10X, L-Histidine 10X, L-Isoleucine 10X, L-Leucine 10X, L-Lysine 10X, L-Methionine 10X, L-Ornithine 10X, L-Proline 10X, L-Serine 10X, L-Tryptophan 10X, L-Tyrosine 10X, L-Valine 10X, Apis Mellifica 200C, Biotin 10X, Epidermis Suis 9C, Galium Aparine 5X, Hamamelis Virginiana 3X, Hepar Suis 6X, Human Growth Hormone 60X, Hypophysis Suis 30C, Natrum Muriaticum 200C, Pantothenic Acid 6X, Phosphoricum Acidum 3X, Riboflavinum 6X, Thuja Occidentalis 200C.

INDICATIONS:

May help revitalize hair, dry skin and nail growth and may temporarily relieve dry, aging skin, brittle nails, slow hair & nail growth, skin blemishes & rashes**

**Claims based on traditional homeopathic practice, not accepted medical evidence. Not FDA evaluated.

WARNINGS:

Do not use if you have ever had an allergic reaction to this product or any of its ingredients.

Ask a doctor before use if you have excessive itching, dryness, redness or swelling of the skin.

Stop use and ask a doctor if symptoms persist for more than 7 days, worsen, or if new symptoms occur.

Keep out of reach of children. In case of overdose, get medical help or call a Poison Control Center right away.

If pregnant or breast feeding, ask a health professional before using product.

Do not use if TAMPER EVIDENT seal around neck of bottle is missing or broken.

Other information:

Store at room temperature.

Keep out of reach of children. In case of overdose, get medical help or call a Poison Control Center right away.

DIRECTIONS:

Adults only: Spray twice under the tongue three times a day.

USES:

May help revitalize hair, dry skin and nail growth and may temporarily relieve dry, aging skin, brittle nails, slow hair & nail growth, skin blemishes & rashes**

**Claims based on traditional homeopathic practice, not accepted medical evidence. Not FDA evaluated.

INACTIVE INGREDIENTS:

Organic alcohol 20% v/v, Purified water.

QUESTIONS:

DIST BY

LIDDELL LABORATORIES INC.

201 APPLE BLVD

WOODBINE, IA 51579

WWW.LIDDELL.NET

1-800-460-7733

PACKAGE LABEL DISPLAY:

DOCTOR FORMULATED

VITÀL
SKIN HAIR
NAILS

May help promote

natural beauty, such as

radiant skin, thick, shiny

hair and longer, stronger

nails.

Readily absorbed. Safe.

No known side effects.

Easy to use.

HOMEOPATHIC
FAST ACTING ORAL SPRAY
LIDDELL
1.0 FL OZ. (30 ml)